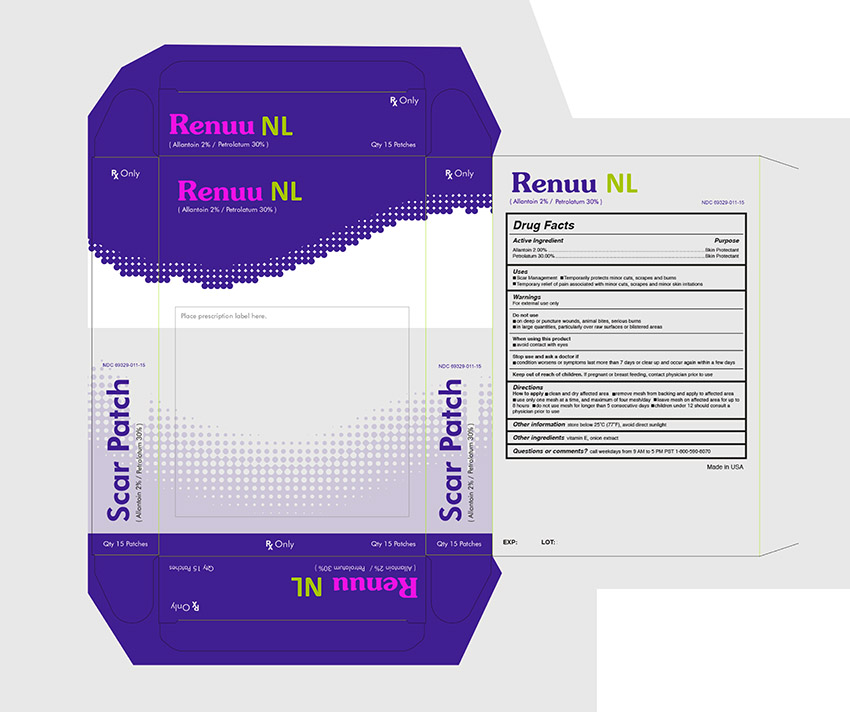 DRUG LABEL: Renuu NL
NDC: 69329-011 | Form: PATCH
Manufacturer: Patchwerx Labs
Category: prescription | Type: HUMAN PRESCRIPTION DRUG LABEL
Date: 20150528

ACTIVE INGREDIENTS: ALLANTOIN 2 g/100 g; PETROLATUM 30 g/100 g
INACTIVE INGREDIENTS: .ALPHA.-TOCOPHEROL; ONION

RENUU NL

INACTIVE INGREDIENT

Other Ingredients vitamin E, Lidocaine, onion extract

Active Ingredient

Allantoin 2.00 %

Petrolatum 30.00 %

Purpose

Skin Protectant

Topical Anesthetic

Skin Protectant

Uses

- Scar Management - Temporarily protects minor cuts , scrapes and burns

- Temporary relief of pain associated with minor cuts, scrapes and minor skin irritations

WARNINGS

For external use only

Do not use

- on deep or puncture wounds, animal bites, serious burns

- in large quantities, particularly over raw surfaces or blistered areas

When using this product

- avoid contact with eyes

Stop use and ask a doctor if

- condition worsens, symptoms persist for more than 7 days or clear up and occur again within a few days

Keep out of reach of children. If pregnant or breastfeeding, contact physician prior to use

Directions

How to apply - clean and dry affected area - remove mesh from backing and apply to affected area

- use only one mesh at a time, and maximum of four mesh / day - leave mesh on affected area for up to

8 hours - children under 12 should consult

physician prior to use

Other information store below 25 C (77 F). avoid direct sunlight

For questions or concerns about this product, please call us - weekdays from 9 AM to 5 PM PST (1) 800-590-8070